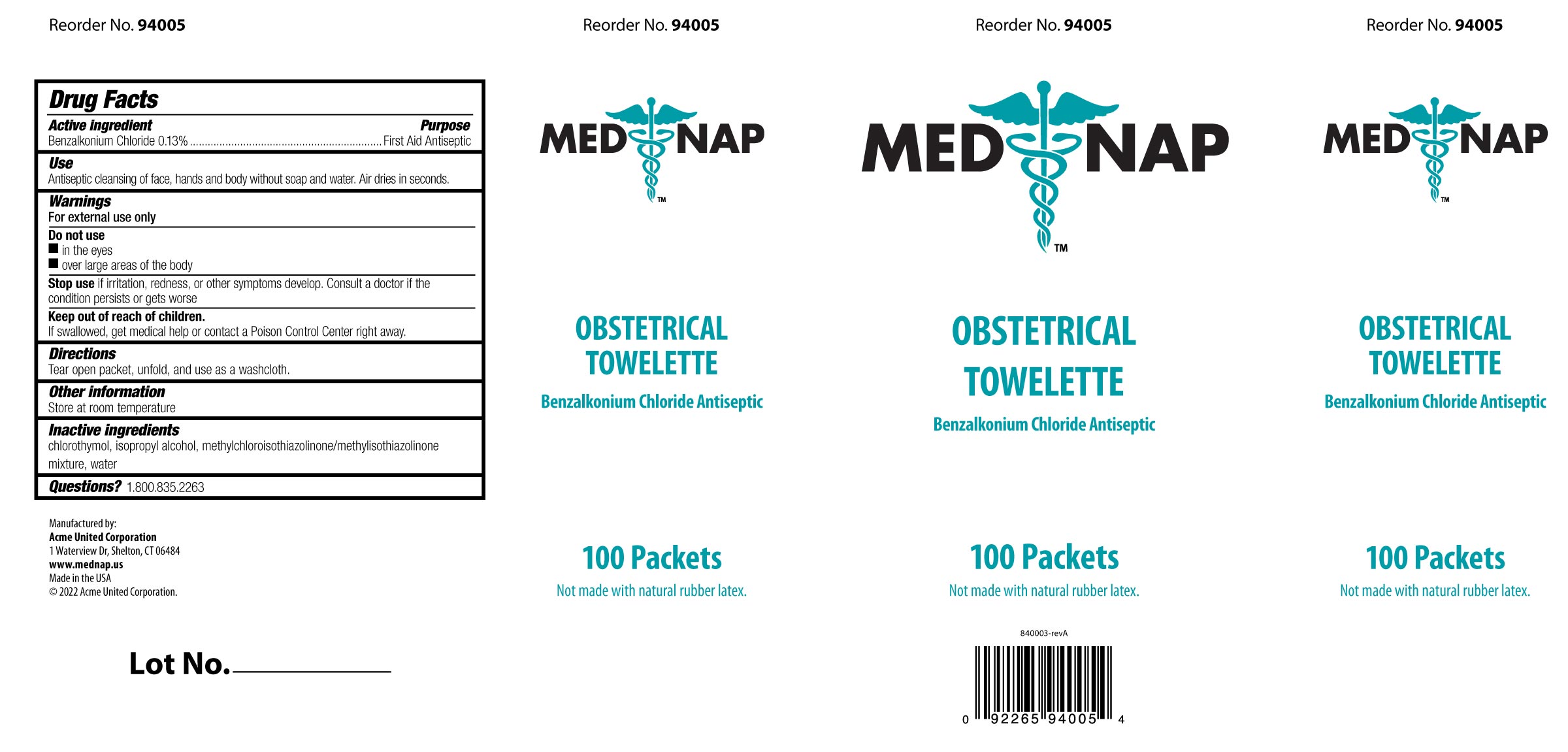 DRUG LABEL: MED NAP Obstetrical Towelette
NDC: 0924-0244 | Form: LIQUID
Manufacturer: Acme United Corporation
Category: otc | Type: HUMAN OTC DRUG LABEL
Date: 20241109

ACTIVE INGREDIENTS: BENZALKONIUM CHLORIDE 0.0018 mg/1.35 mL
INACTIVE INGREDIENTS: WATER; METHYLCHLOROISOTHIAZOLINONE; METHYLISOTHIAZOLINONE; CHLOROTHYMOL; ISOPROPYL ALCOHOL

Med Nap Obstetrical Towelette

Drug Facts Active Ingredient

Benzalkonium Chloride 0.13%

Purpose

First Aid antiseptic

Use:

Antiseptic cleansing of face, hands, and body without soap and water. Air dries in seconds.

Caution:

Keep out of reach of children.

If swallowed, get medical help or contact a Poison Control center right away.

Warnings

For external use only

Do not use ▪in the eyes ▪over large areas of the body

Stop use

Stop use if irritation, redness, or other symptoms develop. Consult a doctor if the condition persists or gets worse.

Directions

Tear open packet, unfold, and use as a washcloth.

Other Information

•Store at room temperature

Inactive Ingredients

chlorothymol, isopropyl alcohol, methylchloroisothiazolinone/methylisothiazolinone mixture, water

Questions? 1.800.835.2263

PACKAGE LABEL

Box Image